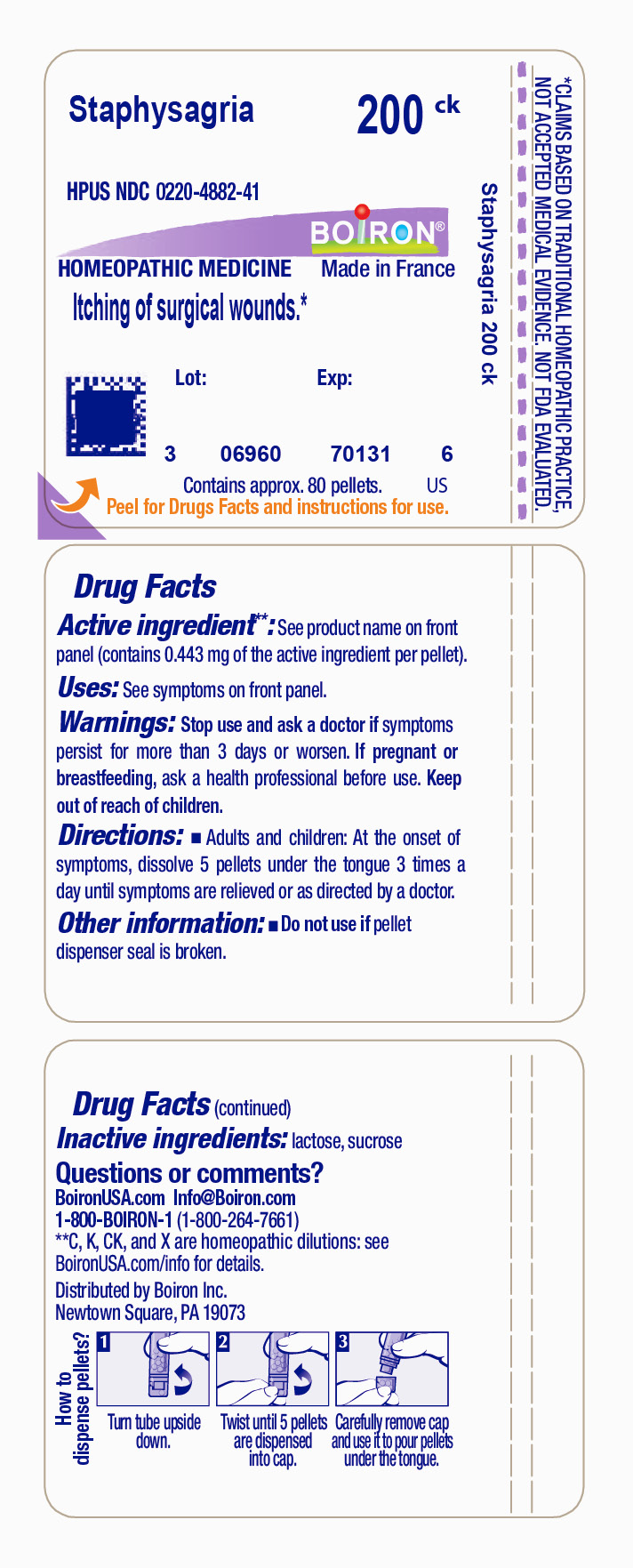 DRUG LABEL: Staphysagria
NDC: 0220-4882 | Form: PELLET
Manufacturer: Boiron
Category: homeopathic | Type: HUMAN OTC DRUG LABEL
Date: 20231115

ACTIVE INGREDIENTS: DELPHINIUM STAPHISAGRIA SEED 200 [kp_C]/200 [kp_C]
INACTIVE INGREDIENTS: SUCROSE; LACTOSE, UNSPECIFIED FORM

Staphysagria 200CK

ACTIVE INGREDIENT

Staphysagria 200CK
(**contains 0.443 mg of the active ingredient per pellet)

INDICATIONS AND USAGE

Itching Of Surgical Wounds*

Stop use and ask a doctor if symptoms persist for more than 3 days or worsen

PREGNANCY OR BREAST FEEDING

If pregnant or breast-feeding ask a health professional before use

Keep out of reach of children

INACTIVE INGREDIENT

lactose, sucrose

DOSAGE AND ADMINISTRATION

Adults and children: At the onset of symptoms, dissolve 5 pellets under the tongue 3 times a day until symptoms are relieved or as directed by a doctor.

QUESTIONS

1-800-BOIRON-1 (1-800-264-7661),
BoironUSA.com Info@boiron.com
Distributed by Boiron, Inc. Newtown Square, PA 19073